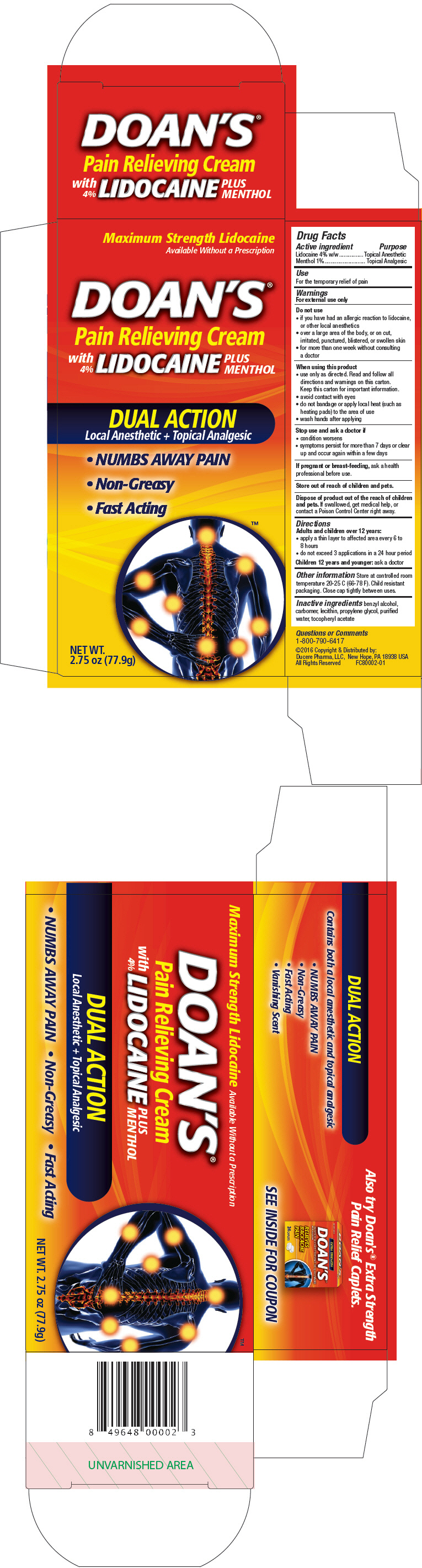 DRUG LABEL: Doans Pain Relieving
NDC: 55741-002 | Form: CREAM
Manufacturer: Dr. Reddy's Laboratories Inc.
Category: otc | Type: HUMAN OTC DRUG LABEL
Date: 20160615

ACTIVE INGREDIENTS: Lidocaine 4 g/100 g; menthol, unspecified form 1 g/100 g
INACTIVE INGREDIENTS: benzyl alcohol; carbomer homopolymer type B (Allyl Pentaerythritol crosslinked); lecithin, soybean; propylene glycol; water; .alpha.-tocopherol acetate

Doan's® Pain Relieving Cream

Drug Facts

ACTIVE INGREDIENT

Active ingredient | Purpose
Lidocaine 4% w/w | Topical Anesthetic
Menthol 1% | Topical Analgesic

Use

For the temporary relief of pain

Warnings

For external use only

Do not use

- if you have had an allergic reaction to lidocaine, or other local anesthetics
- over a large area of the body, or on cut, irritated, punctured, blistered, or swollen skin
- for more than one week without consulting a doctor

When using this product

- use only as directed. Read and follow all directions and warnings on this carton.
  Keep this carton for important information.
- avoid contact with eyes
- do not bandage or apply local heat (such as heating pads) to the area of use
- wash hands after applying

Stop use and ask a doctor if

- condition worsens
- symptoms persist for more than 7 days or clear up and occur again within a few days

PREGNANCY OR BREAST FEEDING

If pregnant or breast-feeding, ask a health professional before use.

Store out of reach of children and pets.

Dispose of product out of the reach of children and pets. If swallowed, get medical help, or contact a Poison Control Center right away.

Directions

Adults and children over 12 years:

- apply a thin layer to affected area every 6 to 8 hours
- do not exceed 3 applications in a 24 hour period

Children 12 years and younger: ask a doctor

Other information

Store at controlled room temperature 20-25 C (66-78 F). Child resistant packaging. Close cap tightly between uses.

Inactive ingredients

benzyl alcohol, carbomer, lecithin, propylene glycol, purified water, tocopheryl acetate

Questions or Comments

1-800-790-6417

PRINCIPAL DISPLAY PANEL - 77.9 g Tube Carton

Maximum Strength Lidocaine

Available Without a Prescription

DOAN'S®
Pain Relieving Cream
with
4%
LIDOCAINE
PLUS
MENTHOL

DUAL ACTION
Local Anesthetic + Topical Analgesic

- NUMBS AWAY PAIN
- Non-Greasy
- Fast Acting

NET WT.
2.75 oz (77.9g)